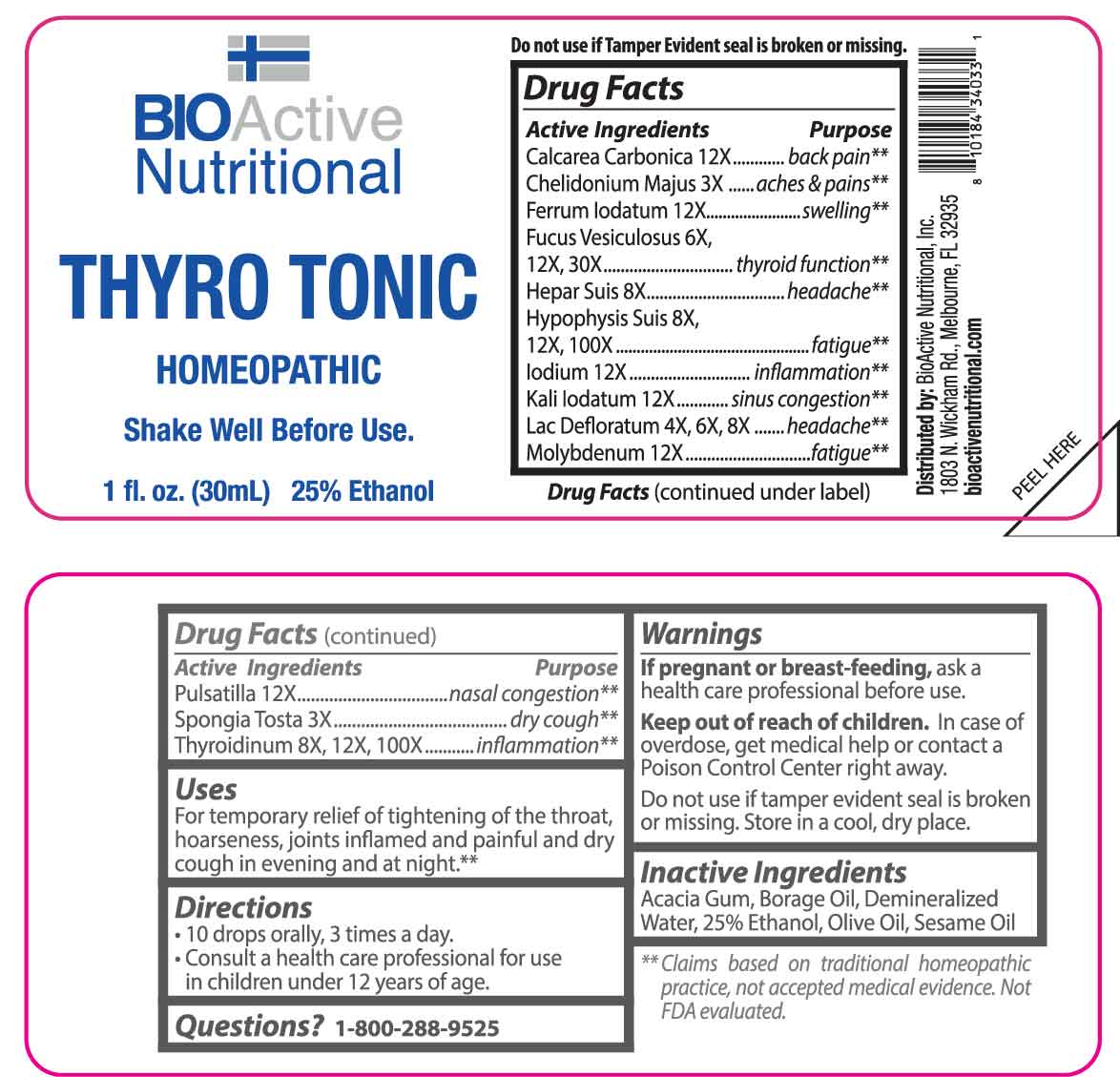 DRUG LABEL: THYRO TONIC
NDC: 43857-0549 | Form: LIQUID
Manufacturer: BioActive Nutritional, Inc.
Category: homeopathic | Type: HUMAN OTC DRUG LABEL
Date: 20250616

ACTIVE INGREDIENTS: CHELIDONIUM MAJUS WHOLE 3 [hp_X]/1 mL; SPONGIA OFFICINALIS SKELETON, ROASTED 3 [hp_X]/1 mL; SKIM MILK 4 [hp_X]/1 mL; FUCUS VESICULOSUS 6 [hp_X]/1 mL; PORK LIVER 8 [hp_X]/1 mL; SUS SCROFA PITUITARY GLAND 8 [hp_X]/1 mL; THYROID 8 [hp_X]/1 mL; OYSTER SHELL CALCIUM CARBONATE, CRUDE 12 [hp_X]/1 mL; FERROUS IODIDE 12 [hp_X]/1 mL; IODINE 12 [hp_X]/1 mL; POTASSIUM IODIDE 12 [hp_X]/1 mL; MOLYBDENUM 12 [hp_X]/1 mL; PULSATILLA PRATENSIS WHOLE 12 [hp_X]/1 mL
INACTIVE INGREDIENTS: ACACIA; BORAGE OIL; OLIVE OIL; SESAME OIL; WATER; ALCOHOL

DRUG FACTS:

ACTIVE INGREDIENTS:

Calcarea Carbonica 12X, Chelidonium Majus 3X, Ferrum Iodatum 12X, Fucus Vesiculosus 6X, 12X, 30X, Hepar Suis 8X, Hypophysis Suis 8X, 12X, 100X, Iodium 12X, Kali Iodatum 12X, Lac Defloratum 4X, 6X, 8X, Molybdenum 12X, Pulsatilla 12X, Spongia Tosta 3X, Thyroidinum 8X, 12X, 100X.

PURPOSE:

Calcarea Carbonica – back pain,** Chelidonium Majus – aches & pains,** Ferrum Iodatum - swelling,** Fucus Vesiculosus – thyroid function,** Hepar Suis - headache,** Hypophysis Suis - fatigue,** Iodium - inflammation,** Kali Iodatum – sinus congestion,** Lac Defloratum - headache,** Molybdenum - fatigue,** Pulsatilla – nasal congestion,** Spongia Tosta – dry cough,** Thyroidinum - inflammation.**

**Claims based on traditional homeopathic practice, not accepted medical evidence. Not FDA evaluated.

USES:

For temporary relief of tightening of the throat, hoarseness, joints inflamed and painful and dry cough in evening and at night.**

**Claims based on traditional homeopathic practice, not accepted medical evidence. Not FDA evaluated.

WARNINGS:

If pregnant or breast-feeding, ask a health care professional before use.

Keep out of reach of children. In case of overdose, get medical help or contact a Poison Control Center right away.

Do not use if tamper evident seal is broken or missing.

Store in a cool, dry place.

KEEP OUT OF REACH OF CHILDREN:

In case of overdose, get medical help or contact a Poison Control Center right away.

DIRECTIONS:

• 10 drops orally, 3 times a day.

• Consult a health care professional for use in children under 12 years of age.

INACTIVE INGREDIENTS:

Arabic Gum, Borage Oil, Demineralized Water, 25% Ethanol, Olive Oil, Sesame Oil

QUESTIONS:

Distributed by:
BioActive Nutritional, Inc.
1803 N. Wickham Rd.
Melbourne, FL 32935
bioactivenutritional.com

1-800-288-9525

PACKAGE LABEL DISPLAY:

BIOActive Nutritional

THYRO TONIC

HOMEOPATHIC

1 fl. oz. (30mL)